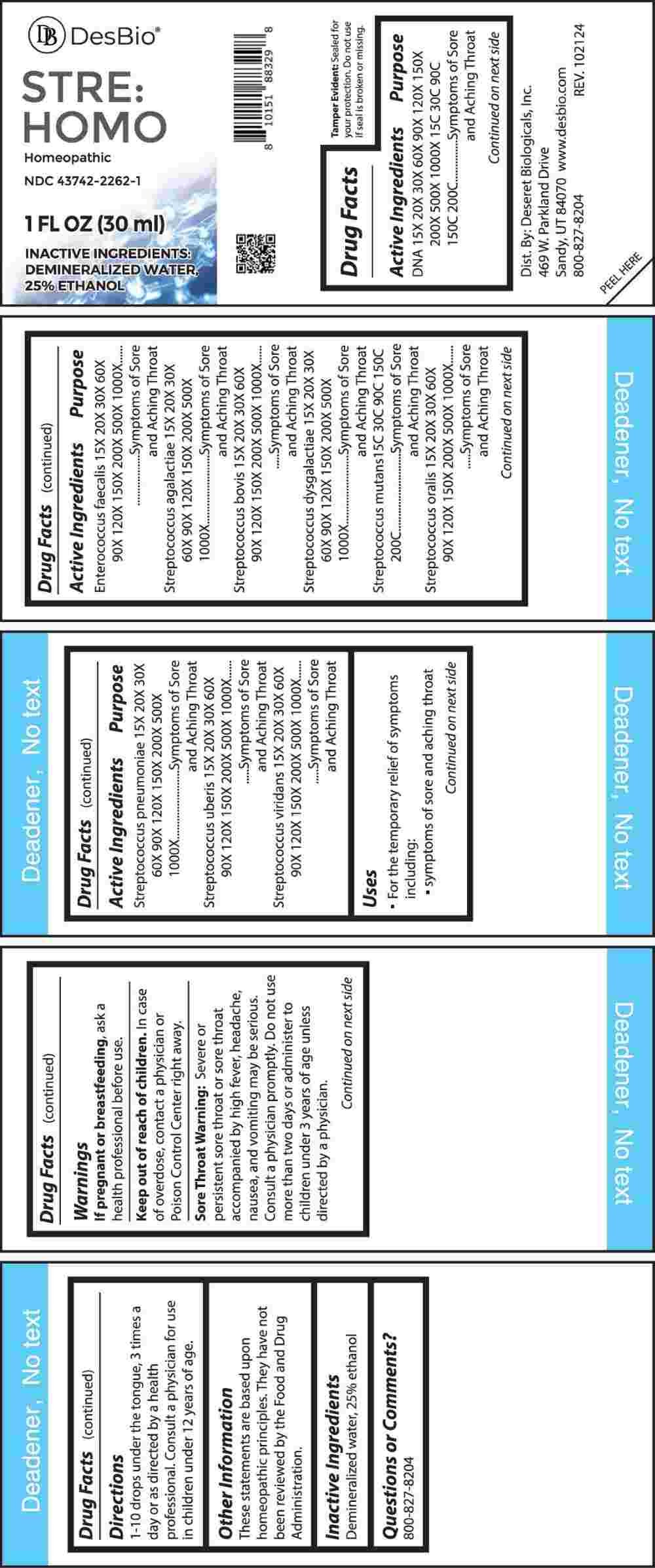 DRUG LABEL: STRE HOMO
NDC: 43742-2262 | Form: LIQUID
Manufacturer: Deseret Biologicals, Inc.
Category: homeopathic | Type: HUMAN OTC DRUG LABEL
Date: 20250409

ACTIVE INGREDIENTS: HERRING SPERM DNA 15 [hp_X]/1 mL; ENTEROCOCCUS FAECALIS 15 [hp_X]/1 mL; STREPTOCOCCUS AGALACTIAE 15 [hp_X]/1 mL; STREPTOCOCCUS EQUINUS 15 [hp_X]/1 mL; STREPTOCOCCUS DYSGALACTIAE 15 [hp_X]/1 mL; STREPTOCOCCUS MUTANS 15 [hp_X]/1 mL; STREPTOCOCCUS ORALIS 15 [hp_X]/1 mL; STREPTOCOCCUS PNEUMONIAE 15 [hp_X]/1 mL; STREPTOCOCCUS UBERIS 15 [hp_X]/1 mL; STREPTOCOCCUS VIRIDANS GROUP 15 [hp_X]/1 mL
INACTIVE INGREDIENTS: WATER; ALCOHOL

DRUG FACTS:

ACTIVE INGREDIENTS:

DNA 15X, 20X, 30X, 60X, 90X, 120X, 150X, 200X, 500X, 1000X, 15C, 30C, 90C, 150C, 200C, Enterococcus Faecalis 15X, 20X, 30X, 60X, 90X, 120X, 150X, 200X, 500X, 1000X, Streptococcus Agalactiae 15X, 20X, 30X, 60X, 90X, 120X, 150X, 200X, 500X, 1000X, Streptococcus Bovis 15X, 20X, 30X, 60X, 90X, 120X, 150X, 200X, 500X, 1000X, Streptococcus Dysgalactiae 15X, 20X, 30X, 60X, 90X, 120X, 150X, 200X, 500X, 1000X, Streptococcus Mutans 15C, 30C, 90C, 150C, 200C, Streptococcus Oralis 15X, 20X, 30X, 60X, 90X, 120X, 150X, 200X, 500X, 1000X, Streptococcus Pneumoniae 15X, 20X, 30X, 60X, 90X, 120X, 150X, 200X, 500X, 1000X, Streptococcus Uberis 15X, 20X, 30X, 60X, 90X, 120X, 150X, 200X, 500X, 1000X, Streptococcus Viridans 15X, 20X, 30X, 60X, 90X, 120X, 150X, 200X, 500X, 1000X.

PURPOSE:

DNA – Symptoms of Sore and Aching Throat, Enterococcus Faecalis - Symptoms of Sore and Aching Throat, Streptococcus Agalactiae - Symptoms of Sore and Aching Throat, Streptococcus Bovis - Symptoms of Sore and Aching Throat, Streptococcus Dysgalactiae - Symptoms of Sore and Aching Throat, Streptococcus Mutans - Symptoms of Sore and Aching Throat, Streptococcus Oralis - Symptoms of Sore and Aching Throat, Streptococcus Pneumoniae - Symptoms of Sore and Aching Throat, Streptococcus Uberis - Symptoms of Sore and Aching Throat, Streptococcus Viridans - Symptoms of Sore and Aching Throat

USES:

• For the temporary relief of symptoms including:

• symptoms of sore and aching throat

These statements are based upon homeopathic principles. They have not been reviewed by the Food and Drug Administration.

WARNINGS:

If pregnant or breastfeeding, ask a health professional before use.

Keep out of reach of children. In case of overdose, contact a physician or Poison Control Center right away.

Sore Throat Warning: Severe or persistent sore throat or sore throat accompanied by high fever, headache, nausea, and vomiting may be serious. Consult a physician promptly. Do not use more that two days or administer to children under 3 years of age unless directed by a physician.

Tamper Evident: Sealed for your protection. Do not use if seal is broken or missing.

KEEP OUT OF REACH OF CHILDREN:

In case of overdose, contact a physician or Poison Control Center right away.

DIRECTIONS:

1-10 drops under the tongue, 3 times a day or as directed by a health professional. Consult a physician for use in children under 12 years of age.

INACTIVE INGREDIENTS:

Demineralized water, 25% ethanol

QUESTIONS:

Dist. By: Deseret Biologicals, Inc.
469 W. Parkland Drive
Sandy, UT 84070

www.desbio.com

800-827-8204

PACKAGE LABEL DISPLAY:

DesBio

STRE:HOMO

Homeopathic

NDC 43742-2262-1

1 FL OZ (30 ml)